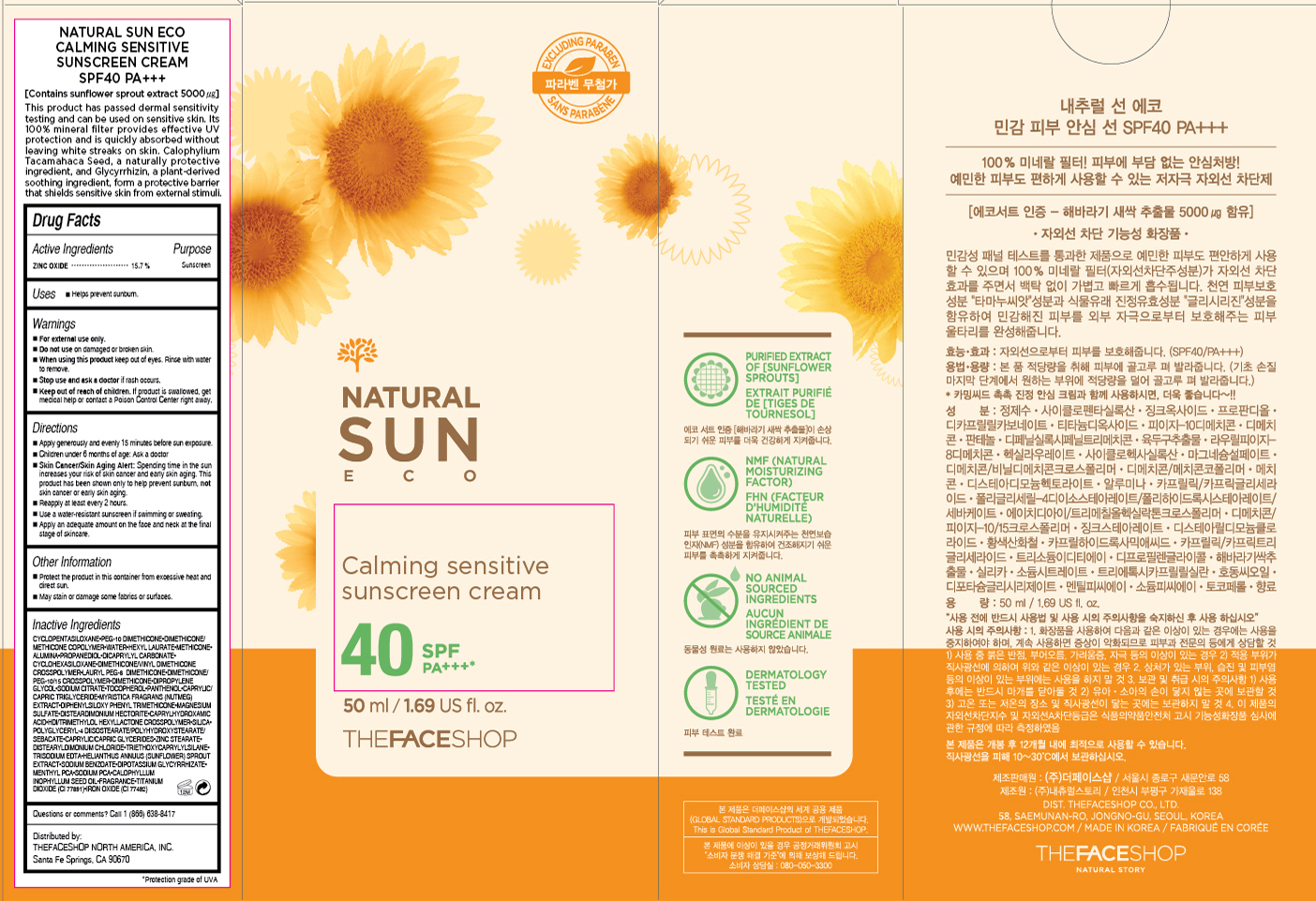 DRUG LABEL: NATURAL SUN ECO
NDC: 51523-178 | Form: CREAM
Manufacturer: THEFACESHOP CO., LTD.
Category: otc | Type: HUMAN OTC DRUG LABEL
Date: 20151001

ACTIVE INGREDIENTS: ZINC OXIDE 7.85 g/50 mL
INACTIVE INGREDIENTS: WATER

NATURAL SUN ECO Calming Sensitive Sunscreen Cream 40 SPF PA+++ 31500178

Active Ingredient

Zinc Oxide 15.7%

Purpose

Sunscreen

Uses:

Helps prevent sunburn.

Warnings

For external use only.

Do not use on damaged or broken skin

When using this product keep out of eyes. Rinse with water to remove.

Stop use and ask a doctor if rash occurs.

Keep out of reach of children. If product is swallowed, get medical help or contact a Poison Control Center right away.

Directions:

Apply generously and evenly 15 minutes before sun exposure.
Children under 6 months of age: Ask a doctor.
Skin Cancer/Skin Aging Alert: Spending time in the sun increases your risk of skin cancer and early skin aging. This product has been shown only to help prevent sunburn, not skin cancer or early skin aging.
Reapply at least every 2 hours.
Use a water-resistant sunscreen if swimming or sweating.

Apply an adequate amount on the face and neck at the final stage of skincare.

OTHER SAFETY INFORMATION

Protect the product in this container from excessive heat and direct sun.

May stain or damage some fabrics or surfaces.

Inactive Ingredients

CYCLOPENTASILOXANE, PEG-10 DIMETHICONE, DIMETHICONE/METHICONE COPOLYMER, WATER, HEXYL LAURATE, METHICONE, ALUMINA, PROPANEDIOL, DICAPRYLYL CARBONATE, CYCLOHEXASILOXANE, DIMETHICONE/VINYL DIMETHICONE CROSSPOLYMER, LAURYL PEG-8 DIMETHICONE, DIMETHICONE/PEG-10/15 CROSSPOLYMER, DIMETHICONE, DIPROPYLENE GLYCOL, SODIUM CITRATE, TOCOPHEROL, PANTHENOL, CAPRYLIC/CAPRIC TRIGLYCERIDE, MYRISTICA FRAGRANS (NUTMEG) EXTRACT, DIPHENYLSILOXY PHENYL TRIMETHICONE, MAGNESIUM SULFATE, DISTEARDIMONIUM HECTORITE, CAPRYLHYDROXAMIC ACID, HDI/TRIMETHYLOL HEXYLLACTONE CROSSPOLYMER, SILICA, POLYGLYCERYL-4 DIISOSTEARATE/POLYHYDROXYSTEARATE/SEBACATE, CAPRYLIC/CAPRIC GLYCERIDES, ZINC STEARATE, DISTEARYLDIMONIUM CHLORIDE, TRIETHOXYCAPRYLYLSILANE, TRISODIUM EDTA, HELIANTHUS ANNUUS (SUNFLOWER) SPROUT EXTRACT, SODIUM BENZOATE, DIPOTASSIUM GLYCYRRHIZATE, MENTHYL PCA, SODIUM PCA, CALOPHYLLUM INOPHYLLUM SEED OIL, FRAGRANCE, TITANIUM DIOXIDE (CI 77891), IRON OXIDE (CI 77492)

Questions or comments? Call 1-866-638-8417

Distributed by:

THEFACESHOP NORTH AMERICA, INC.

Santa Fe Springs, CA 90670

PACKAGE LABEL

NATURAL SUN ECO

Calming Sensitive Sunscreen Cream

40 SPF PA+++

Contains sunflower sprout extract 5000 µg

This product has passed dermal sensitivity testing and can be used on sensitive skin.

Its 100 % mineral filter provides effective UV protecxtion and is quickly absorbed without leaving white streaks on skin.

Calophyllum Tacamahaca Seed, a naturally protetive ingredient, and Glycyrrhizin,

a plant-derived barrier that shileds sensitive skin from external stimuli.